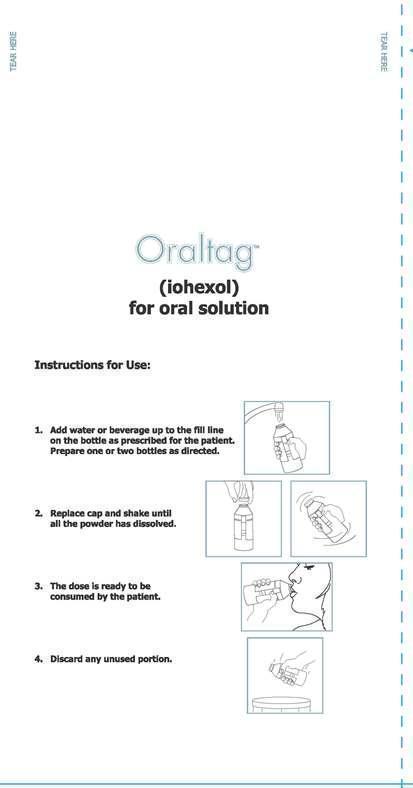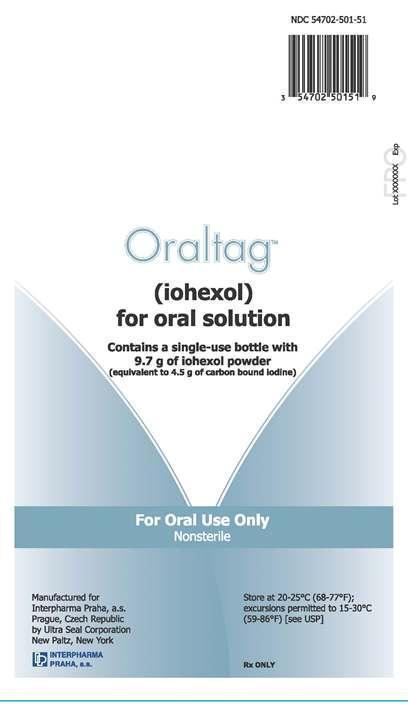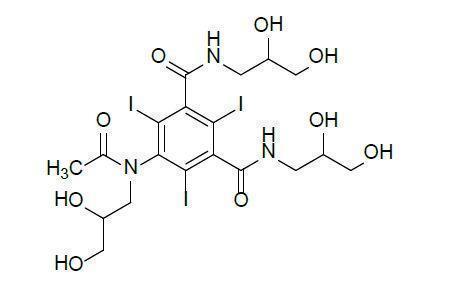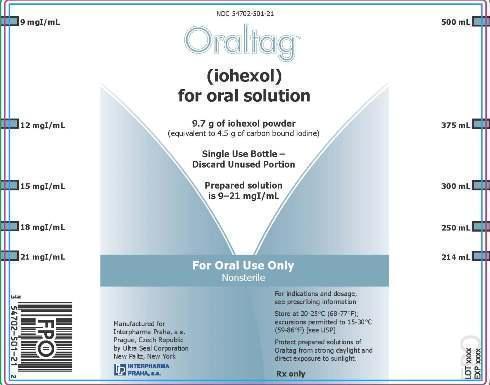 DRUG LABEL: ORALTAG
NDC: 54702-501 | Form: FOR SOLUTION
Manufacturer: Interpharma Praha, a.s.
Category: prescription | Type: HUMAN PRESCRIPTION DRUG LABEL
Date: 20230105

ACTIVE INGREDIENTS: IOHEXOL 4.5 g/1 1

HIGHLIGHTS OF PRESCRIBING INFORMATION

These highlights do not include all the information needed to use ORALTAG safely and effectively. See full prescribing information for ORALTAG.
ORALTAG™ (iohexol) for oral solution
Initial U.S. Approval: 1985

1 INDICATIONS AND USAGE

Oraltag is a radiographic contrast agent indicated for use in opacification of the gastrointestinal tract during computed tomography (CT) of the abdomen and pelvis (1)

Limitations of Use

Not indicated for diagnostic examination of the gastrointestinal tract (1)

2 DOSAGE AND ADMINISTRATION

For oral use only:

- Adults: 1 to 2 bottles (4.5 g to 9 g iodine (I)) (2)
- Pediatric patients 3 to 18 years of age: less than 1 bottle to 2 bottles (less than 4.5 gI up to 9 gI) (2)
- Pediatric patients less than 3 years of age: up to 1 bottle (4.5 gI) (2)

3 DOSAGE FORMS AND STRENGTHS

For oral solution: Each single use bottle contains 9.7 g iohexol (equivalent to 4.5 g carbon bound iodine)

4 CONTRAINDICATIONS

Hypersensitivity to iodinated contrast agents, including iohexol

5 WARNINGS AND PRECAUTIONS

- Hypersensitivity reactions: life-threatening or fatal reactions can occur. Resuscitation equipment and personnel should be available (5.2)
- Thyroid function test alterations: Oraltag may alter tests which depend on iodine estimation. Perform such tests prior to Oraltag administration (5.3)

6 ADVERSE REACTIONS

The most common adverse reactions (incidence < 2%) are nausea, vomiting, and diarrhea (6)

To report SUSPECTED ADVERSE REACTIONS, contact Interpharma Praha at 1-877-886-7040 or FDA at 1-800-FDA-1088 or www.fda.gov/medwatch.

FULL PRESCRIBING INFORMATION

1 INDICATIONS AND USAGE

Oraltag is indicated for use in computed tomography of the abdomen and pelvis to opacify bowel loops and delineate between normal loops and adjacent organs or areas of suspected pathology.

Limitations of Use

Oraltag is not indicated for diagnostic examination of the gastrointestinal tract.

2 DOSAGE AND ADMINISTRATION

2.1 Recommended Dosing

For oral use only [see Warnings and Precautions (5.1)]

Refer to Table 1 for dosing information.

Table 1 Dosing Guidelines for Oraltag

Patient Age | Recommended Dose [Total volume of Oraltag administered will vary depending on the size of the patient] | Volume of Prepared Solution to Administer (at a concentration of 9 mgI per mL) | Maximum Total Iodine Dose
Adults | Administer 4.5 g to 9 g of iodine (1 to 2 bottles of prepared solution), orally | 500 mL to 1000 mL | 9 grams
3 to 18 years of age | Administer up to 9 g of iodine (from less than 1 bottle up to 2 bottles of prepared solution), orally | 280 mL to 750 mL, depending on size of patient | 9 grams
Less than 3 years of age | Administer up to 4.5 g of iodine (portion of 1 bottle of prepared solution), orally | 120 mL to 300 mL, depending on size of patient | 4.5 grams

The variables of patient age, weight, or medical condition, may require adjustment of the concentration and/or volume of solution to be prepared for administration. If it is anticipated that the patient will have difficulty in consuming the required volume, a higher concentration of solution (up to 21 mgI per mL) can be prepared and a smaller volume administered (see Table 2).

Table 2 Preparation of Higher Concentrations of Oraltag at Lower Volumes

For Final Concentration (mgI/mL) | Add Water or a Beverage [Examples include infant formula, milk, juice, carbonated beverage or a sports drink] to the Indicated Mark on the Bottle; (mL)
9 | 500
12 | 375
15 | 300
18 | 250
21 | 214

2.2 Preparation and Administration Instructions

- Reconstitute Oraltag, supplied as a powder in a single use bottle, with water or other beverages just before its use
- Do not mix other pharmaceuticals with Oraltag
- Use the 5 fill lines premolded and labeled on the bottle to determine the volume for the 5 target concentrations (9, 12, 15, 18, and 21 mgI/mL)
- Administer Oraltag 20 to 60 minutes before image acquisition
- Protect prepared solution from strong daylight and direct exposure to sunlight
- Discard any unused portions

3 DOSAGE FORMS AND STRENGTHS

For oral solution: Oraltag is provided as a white to off-white powder of 9.7 g iohexol, (equivalent to 4.5 g of carbon bound iodine) in a single-use bottle.

4 CONTRAINDICATIONS

Oraltag is contraindicated in patients with a known hypersensitivity to iodinated contrast agents, including iohexol [see Warnings and Precautions (5.2)] .

5 WARNINGS AND PRECAUTIONS

5.1 Risks Associated with Inadvertent Parenteral Administration

Oraltag is not a sterile product and is not suitable for a parenteral route of administration. Serious adverse reactions such as sepsis can occur if administered parenterally. Do not administer Oraltag parenterally.

5.2 Hypersensitivity Reactions

Administration of Oraltag can cause life-threatening hypersensitivity reactions including anaphylaxis [see Contraindications (4)] . Patients at increased risk include those with a previous reaction to an iodinated contrast agent and allergic disorders (i.e., bronchial asthma, allergic rhinitis, and food allergies). Emergency resuscitation equipment and trained personnel should be available.

5.3 Alteration of Thyroid Function Tests

Iodinated contrast agents may alter the results of thyroid function tests which depend on iodine estimation, e.g., radioactive iodine uptake test. Therefore, such testing, if indicated, should be performed prior to the administration of this preparation.

6 ADVERSE REACTIONS

The following adverse reactions are described in greater detail in other sections:

- Hypersensitivity reactions [see Warnings and Precautions (5.2)]

6.1 Clinical Trials Experience

In studies involving 44 adult and 69 pediatric patients who received oral and intravenous iohexol for CT examinations of the abdomen, two reports of vomiting (2%) were noted.

6.2 Postmarketing Experience

Because these reactions are reported voluntarily from a population of uncertain size, it is not always possible to reliably estimate their frequency or establish a causal relationship to drug exposure.

The following adverse reactions have been reported following oral administration of the dilute, hypotonic solutions of iohexol (9 mgI/mL to 21 mgI/mL):

- Gastrointestinal: nausea, diarrhea

8 USE IN SPECIFIC POPULATIONS

8.1 Pregnancy

Risk Summary

There are no human data on risks associated with the use of Oraltag during pregnancy. The background risk in the U.S. general population of major birth defects is 2% to 4% and risk of miscarriage is 15% to 20% of clinically recognized pregnancies. In animal reproduction studies, no evidence of fetal harm was observed with intravenous administration of iohexol to rats and rabbits at doses up to 100 times the maximum recommended human intravenous dose.

8.2 Lactation

Risk Summary

Iohexol administered intravenously is present in human milk at concentrations approximately 0.5% of the maternal dose; however, it is not known to what extent iohexol administered orally is present in human milk. Iodinated contrast is poorly excreted into human milk and is poorly absorbed by the gastrointestinal tract of a breastfed infant. The developmental and health benefits of breastfeeding should be considered along with the mother's clinical need for Oraltag and any potential adverse effects on the breastfed infant from Oraltag.

Clinical Considerations

Interruption of breastfeeding after exposure to iodinated contrast media is not necessary because the potential exposure of the breastfed infant to iodine is small. However, a lactating woman may consider interrupting breastfeeding and pumping and discarding breast milk for 10 hours (approximately 5 half-lives) after Oraltag administration in order to minimize potential drug exposure to a breastfed infant.

8.4 Pediatric Use

The safety and effectiveness of oral iohexol have been established in pediatric patients.

8.5 Geriatric Use

In general, dose selection for an elderly patient should be cautious, usually starting at the low end of the dosing range, reflecting the greater frequency of decreased hepatic, renal, or cardiac function, and of concomitant disease or other drug therapy.

11 DESCRIPTION

Oraltag (iohexol) is a radiographic contrast agent for oral solution. Oraltag is provided as a nonsterile white to off-white powder with 9.7 g iohexol (equivalent to 4.5 g of carbon bound iodine) in a 20-ounce beverage bottle. Each bottle is individually sealed in a foil laminated pouch. Oraltag consists of 100 percent iohexol and contains no excipients.

Iohexol is designated chemically as N,N´-bis(2,3-dihydroxypropyl)-5-[N-(2,3-dihydroxypropyl)acetamido]-2,4,6-triiodoisophthalamide. It is a nonionic, water-soluble iodinated contrast medium with a molecular weight of 821.14 (carbon bound iodine content 46.36%). In aqueous solution each triiodinated molecule remains undissociated.

The chemical structure is:

Oraltag, when prepared at a concentration of 9 mgI/mL in water, has an osmolality of 30 mOsmol/kg water. The calculated osmolality of 21 mgI/mL in water is 55 mOsmol/kg water. The prepared solutions are hypotonic.

12 CLINICAL PHARMACOLOGY

12.1 Mechanism of Action

Iohexol enhances imaging due to its high iodine content attenuating the beam of X-rays during CT examinations. Different tissues within the body attenuate X-rays to different degrees, and oral administration of iohexol allows for enhanced visualization due to the iodine present in bowel loops.

12.3 Pharmacokinetics

Orally administered iohexol is very poorly absorbed from the normal gastrointestinal tract. Only 0.1 to 0.5% of the oral dose is excreted by the kidneys. This amount may increase in the presence of bowel perforation, bowel obstruction, or severe inflammatory bowel disease.

Iohexol displays a low affinity for serum or plasma proteins and is poorly bound to serum albumin. No significant metabolism, deiodination or biotransformation occurs.

13 NONCLINICAL TOXICOLOGY

13.1 Carcinogenesis, Mutagenesis, Impairment of Fertility

No long-term animal studies have been performed to evaluate carcinogenic potential or mutagenesis.

In animal reproduction studies, no evidence of impaired fertility was observed with intravenous administration of iohexol to rats and rabbits at doses up to 100 times the maximum recommended human intravenous dose.

16 HOW SUPPLIED/STORAGE AND HANDLING

How Supplied

Oraltag is supplied as a nonsterile white to off-white powder for oral solution in a single-use 20-ounce polyethylene terephthalate beverage bottle closed with a lined polypropylene cap. Each bottle is packaged in a sealed foil pouch.

Twelve (12) bottles per pack (NDC 54702-501-52).

Twenty-five (25) bottles per pack (NDC 54702-501-62).

Storage

Store at controlled room temperature, 20° to 25°C (68° to 77°F); excursions permitted to 15° to 30°C (59° to 86°F) [see USP Controlled Room Temperature].

Protect prepared solutions of Oraltag from strong daylight and direct exposure to sunlight.

Do not use if tamper-evident foil pouch has been opened.

17 PATIENT COUNSELING INFORMATION

Hypersensitivity Reactions

Advise patients about the risk of hypersensitivity reactions to Oraltag and the need to notify their healthcare provider if signs or symptoms of hypersensitivity reaction occur [see Warnings and Precautions (5.2)] .

Manufactured for Interpharma Praha, a.s., Prague, Czech Republic by Ultra Seal Corporation, New Paltz, New York.

PRINCIPAL DISPLAY PANEL - 9.7 g Bottle Label

NDC 54702-501-21

Oraltag™

(iohexol) for oral solution

9.7 g of iohexol powder
(equivalent to 4.5 g of carbon bound iodine)

Single Use Bottle - Discard Unused Portion

Prepared solution is 9-21 mgI/mL

For Oral Use Only
Nonsterile

For indications and dosage, see prescribing information.

Store at 20-25˚C (68-77˚F); excursions permitted to 15-30˚C (59-86˚F) [see USP]

Protect prepared solutions of Oraltag from strong daylight and direct exposure to sunlight.

Rx Only

Manufactured for Interpharma Praha, a.s.
Prague, Czech Republic
by Ultra Seal Corporation
New Paltz, New York

PRINCIPAL DISPLAY PANEL - Foil Pouch Label

NDC 54702-501-51

Oraltag™

(iohexol) for oral solution

Contains a single-use bottle with 9.7 g of iohexol powder
(equivalent to 4.5 g of carbon bound iodine)

For Oral Use Only
Nonsterile

Store at 20-25˚C (68-77˚F); excursions permitted to 15-30˚C (59-86˚F) [see USP]

Rx Only

Manufactured for Interpharma Praha, a.s.
Prague, Czech Republic
by Ultra Seal Corporation
New Paltz, New York

Instructions for Use:

1. Add water or beverage up to the fill line on the bottle as prescribed for the patient. Prepare one or two bottles as directed.

2. Replace cap and shake until all the powder has dissolved.

3. The dose is ready to be consumed by the patient.

4. Discard any unused portion.